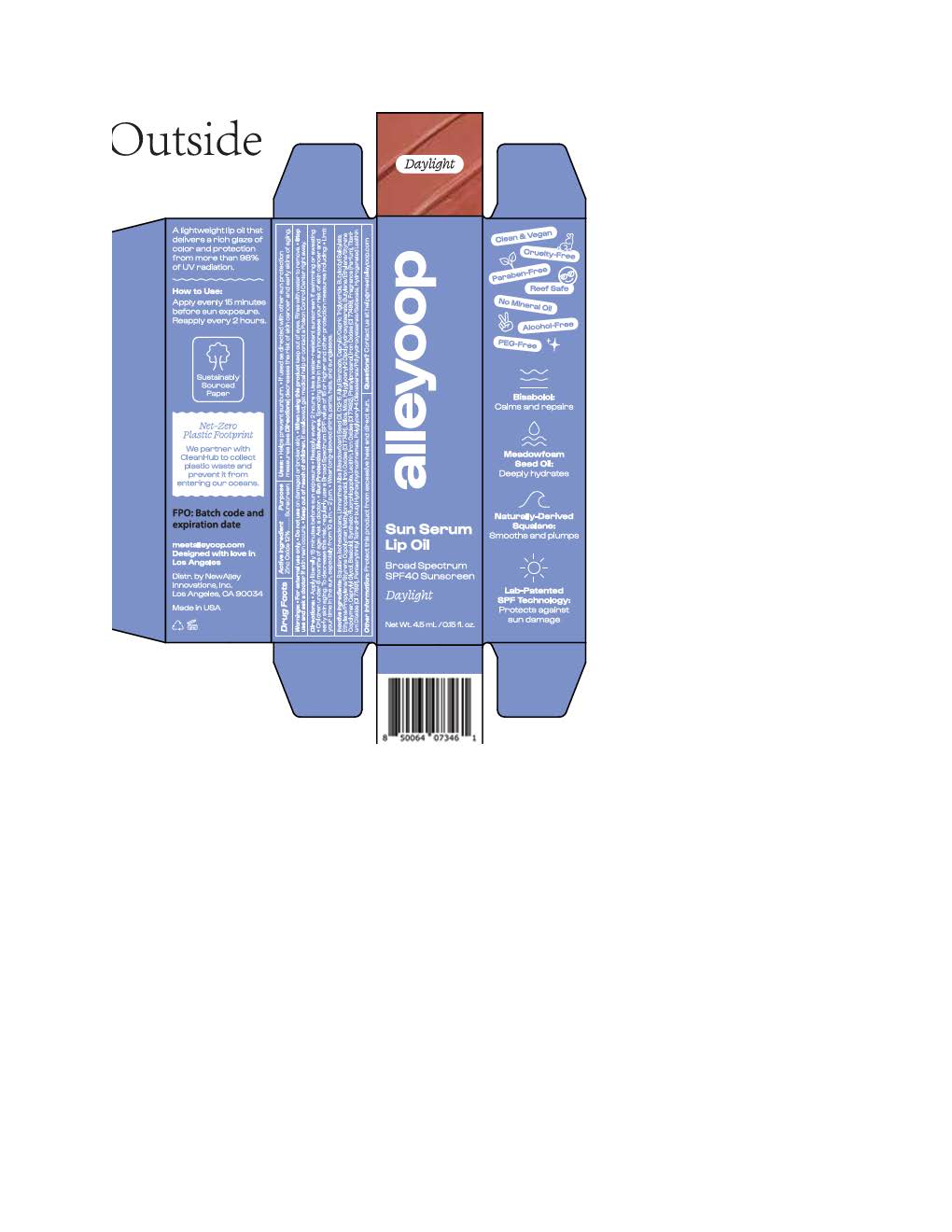 DRUG LABEL: Alleyoop Sun Serum Lip Oil
NDC: 84830-2107 | Form: LOTION
Manufacturer: NewAlley Innovations Inc
Category: otc | Type: HUMAN OTC DRUG LABEL
Date: 20250924

ACTIVE INGREDIENTS: ZINC OXIDE 132 mg/1 mL
INACTIVE INGREDIENTS: MICA; TITANIUM DIOXIDE; FERRIC OXIDE YELLOW; FERROSOFERRIC OXIDE; METHYLPROPANEDIOL; LECITHIN, SOYBEAN; SQUALANE; BUTYLOCTYL SALICYLATE; PHENYLPROPANOL; PENTAERYTHRITYL TETRA-DI-T-BUTYL HYDROXYHYDROCINNAMATE; ISOHEXADECANE; .ALPHA.-BISABOLOL, (+)-; FERRIC OXIDE RED; ALKYL (C12-15) BENZOATE; CAPRYLIC/CAPRIC TRIGLYCERIDE; CAPRYLYL GLYCOL; POLYGLYCERYL-4 DIISOSTEARATE/POLYHYDROXYSTEARATE/SEBACATE; LIMNANTHES ALBA (MEADOWFOAM) SEED OIL; SILICON DIOXIDE

Alleyoop Sun Serum Lip Oil